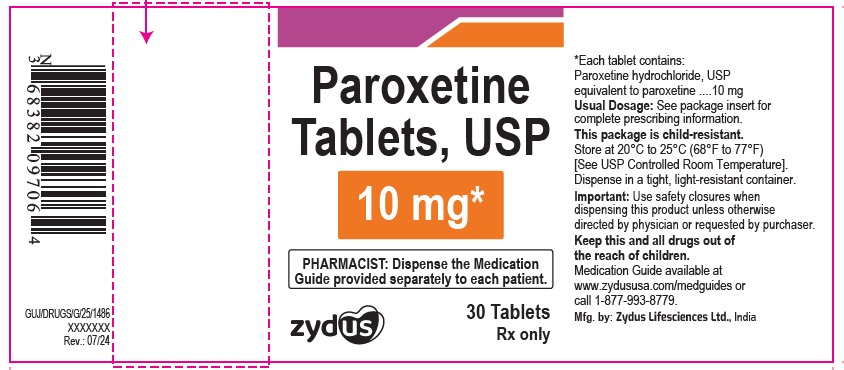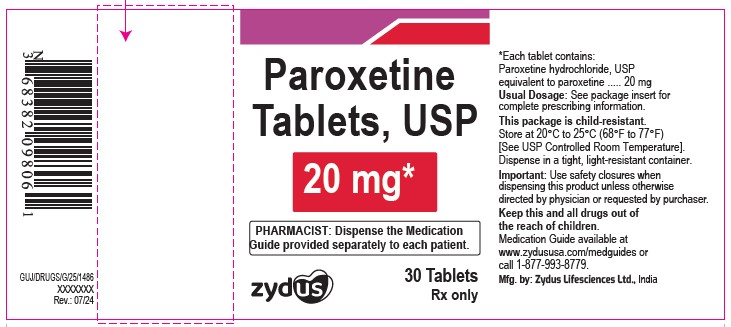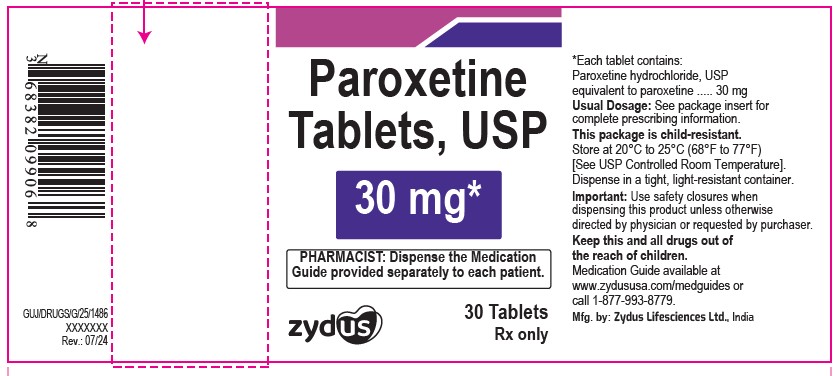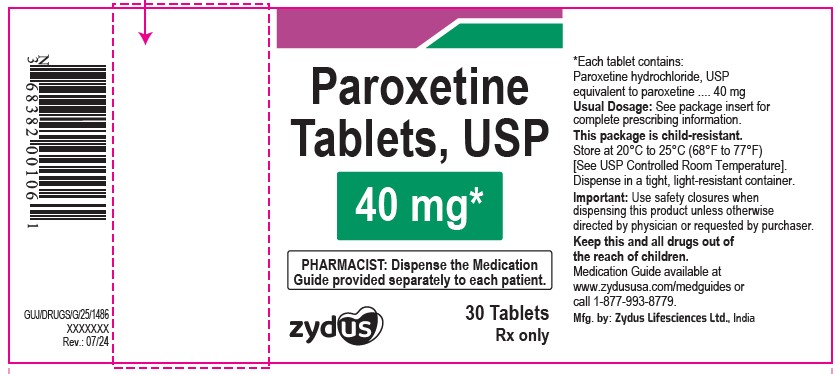 DRUG LABEL: Paroxetine
NDC: 65841-097 | Form: TABLET, FILM COATED
Manufacturer: Zydus Lifesciences Limited
Category: prescription | Type: HUMAN PRESCRIPTION DRUG LABEL
Date: 20241203

ACTIVE INGREDIENTS: PAROXETINE HYDROCHLORIDE ANHYDROUS 10 mg/1 1
INACTIVE INGREDIENTS: ANHYDROUS DIBASIC CALCIUM PHOSPHATE; ANHYDROUS LACTOSE; HYPROMELLOSES; MAGNESIUM STEARATE; POLYETHYLENE GLYCOL 6000; SODIUM STARCH GLYCOLATE TYPE A POTATO; POVIDONE; TALC; TITANIUM DIOXIDE

Paroxetine Tablets, USP

PACKAGE LABEL.PRINCIPAL DISPLAY PANEL

NDC 65841-097-06 in pack count of 30 tablets

Paroxetine Tablets USP, 10 mg

Rx only

30 tablets

NDC 65841-098-06 in pack count of 30 tablets

Paroxetine Tablets USP, 20 mg

Rx only

30 tablets

NDC 65841-099-06 in pack count of 30 tablets

Paroxetine Tablets USP, 30 mg

Rx only

30 tablets

NDC 65841-601-06 in pack count of 30 tablets

Paroxetine Tablets USP, 40 mg

Rx only

30 tablets